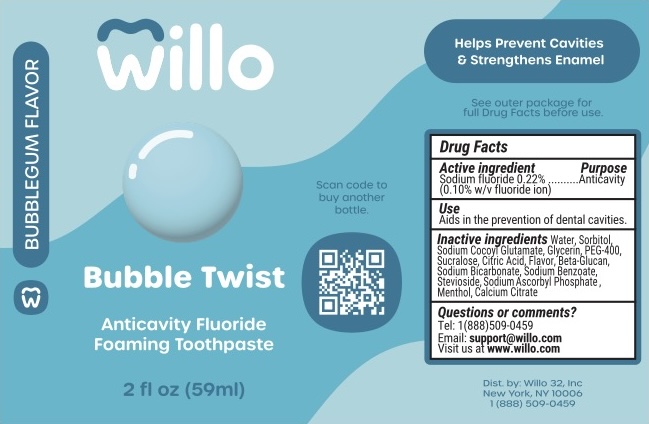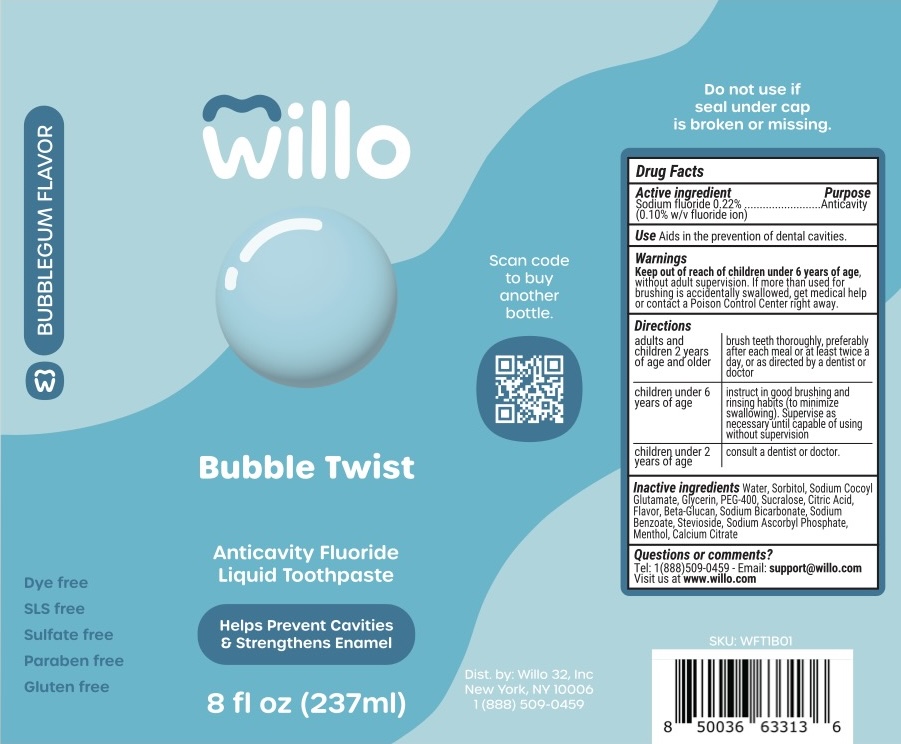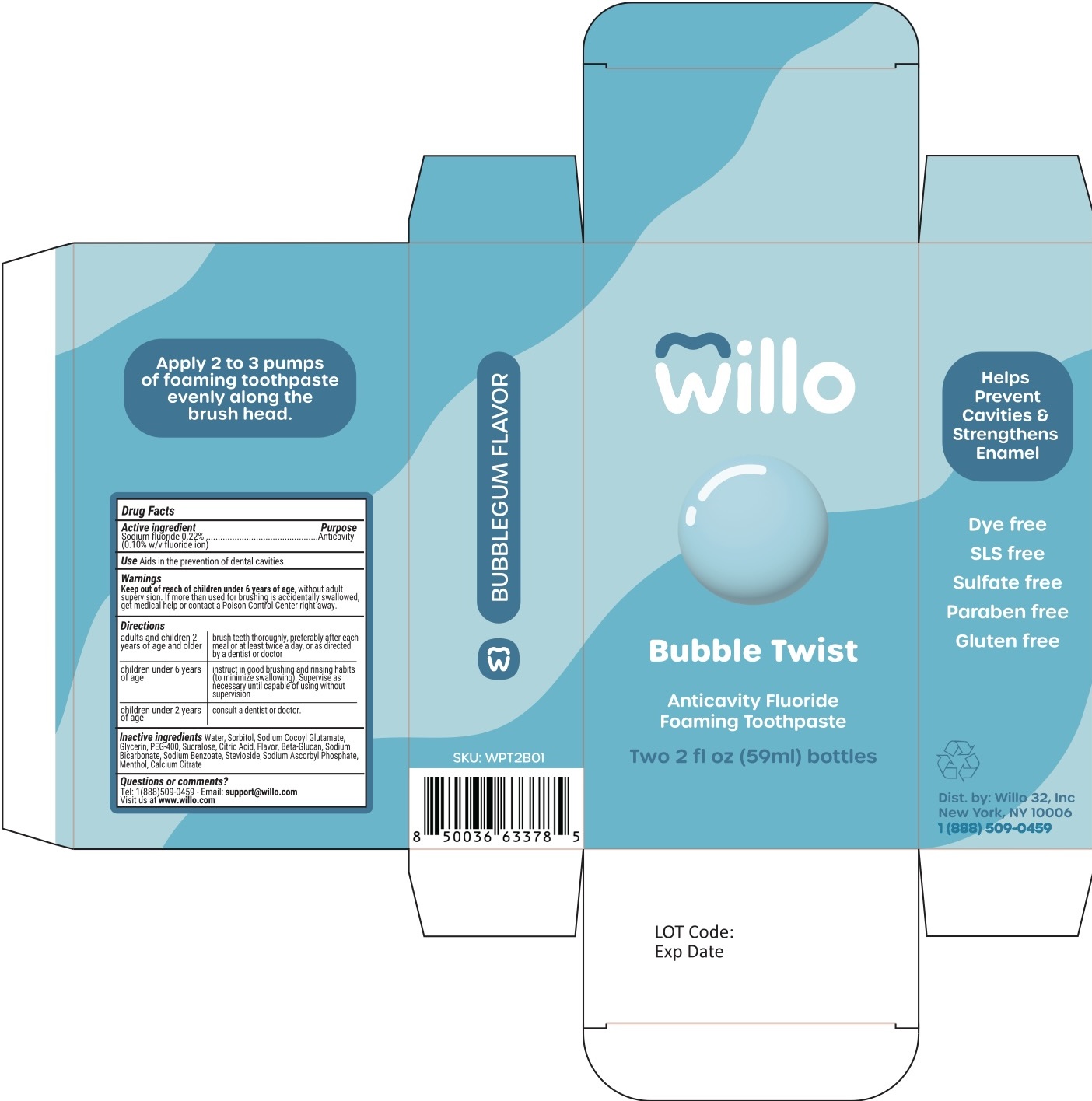 DRUG LABEL: Willo Bubble Twist
NDC: 84185-102 | Form: PASTE, DENTIFRICE
Manufacturer: Willo 32 Inc
Category: otc | Type: HUMAN OTC DRUG LABEL
Date: 20251111

ACTIVE INGREDIENTS: SODIUM FLUORIDE 1 mg/1 mL
INACTIVE INGREDIENTS: SODIUM BENZOATE; CALCIUM CITRATE; STEVIOSIDE; SODIUM BICARBONATE; SODIUM COCOYL GLUTAMATE; WATER; SUCRALOSE; SORBITOL; GLYCERIN; YEAST .BETA.-D-GLUCAN; MENTHOL; CITRIC ACID; SODIUM ASCORBYL PHOSPHATE; PEG-400

Willo Bubble Twist Dye Free 8 oz

Drug Facts

Active Ingredient

Sodium Fluoride 0.22%

(0.10% w/v Fluoride Ion)

Purpose Section

Purpose

Anticavity

Use Section

Use

Aids in the prevention of dental cavities

Warnings

Keep out of reach of children under 6 years of age, without adult supervision. If more than used for brushing is accidentally swallowed, get medical help or contact a Poison Control Center right away.

Directions

adults and; children 2 years; of age and older | brush teeth thoroughly, preferably; after each meal or at least twice a; day, or as directed by a dentist or; doctor
children under 6; years of age | instruct in good brushing and; rinsing habits (to minimize swallowing). Supervise as; necessary until capable of using; without supervision
children under 2; years of age | consult a dentist or doctor.

Inactive Ingredients

Water, Sorbitol, Sodium Cocoyl Glutamate, Glycerin, PEG-400, Sucralose, Citric Acid, Flavor, Beta-Glucan, Sodium Bicarbonate, Sodium Benzoate, Stevioside, Sodium Ascorbyl Phosphate, Menthol, Calcium Citrate

Questions or comments?

Tel: 1(888) 509-0459 or Email: support@willo.com

Visit us at willo.com

Distributed by: Willo 32, Inc.

New York NY 10016

Willo.com

Flavor description

BUBBLEGUM FLAVOR

Free of claims

Dye free

SLS free

Sulfate free

Paraben free

Gluten free

Distributor name and address

Dist. by: Willo 32, Inc

New York, NY 10006

1 (888) 509-0459

Broken seal warning

Do not use if

seal under cap

is broken or missing.

Willo Bubble Twist 8 oz Label

Willo

Bubble Twist

Anticavity Fluoride Liquid Toothpaste

Helps Prevent Cavities

& Strengthens Enamel

8 fl oz (237 ml)